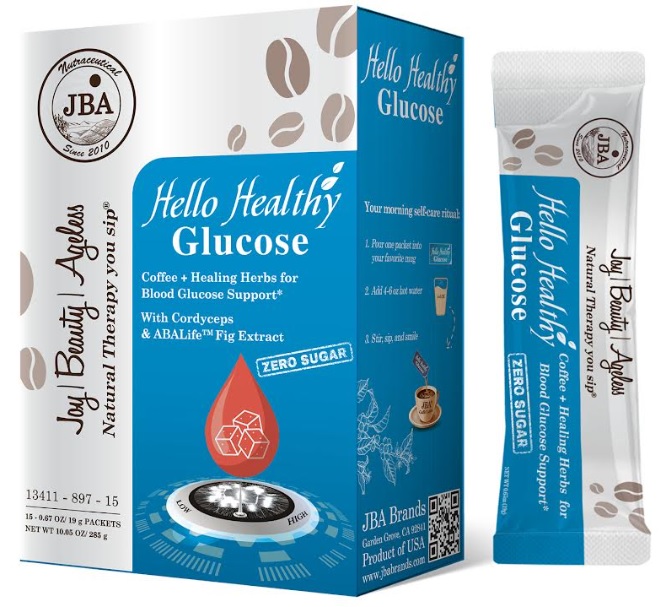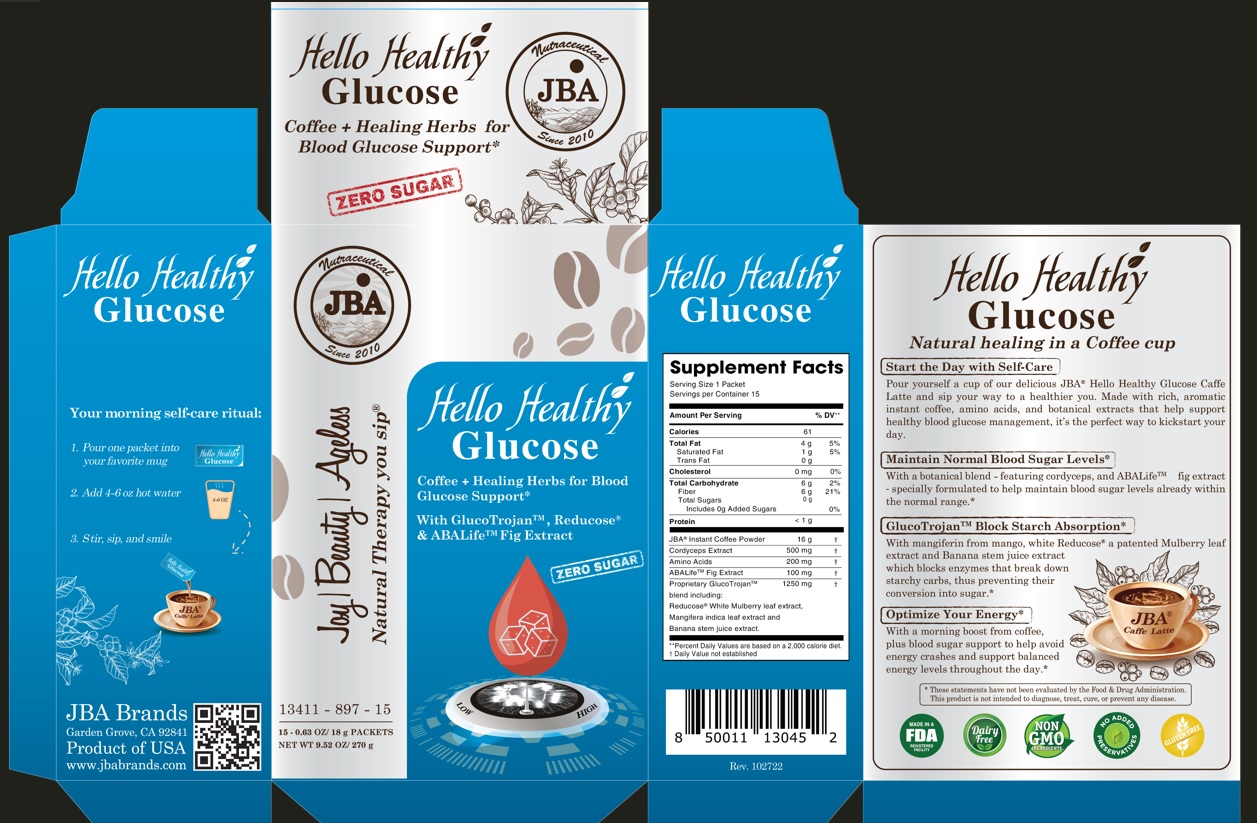 DRUG LABEL: JBA Hello Healthy Glucose Coffee Healing Herbs for Blood Glucose Support With GlucoTrojan Reducose and ABALife Fig Extract
NDC: 13411-897 | Form: POWDER
Manufacturer: Advanced Pharmaceutical Services, Inc. Dba Affordable Quality Pharmaceuticals
Category: other | Type: DIETARY SUPPLEMENT
Date: 20230222

ACTIVE INGREDIENTS: COFFEE BEAN 16 g/18 g; OPHIOCORDYCEPS SINENSIS 500 mg/18 g; AMINO ACIDS, SOURCE UNSPECIFIED 200 mg/18 g; CLUSTER FIG 100 mg/18 g; MANGO 500 mg/18 g; BANANA 500 mg/18 g; WHITE MULBERRY 250 mg/18 g

Identity

Dietary supplement

Warnings

- Keep out of reach of children
- Do not exceed the recommended dose
- Consult your physician prior to using this product if you are pregnant, nursing, or if you are taking blood glucose lowering medication, or have a medical condition.

Direction

Your morning self-care ritual:

- Pour one packet into your favorite mug
- Add 4-6 oz hot water
- Stir, sip and smile

Safe handling warning

- Store in a cool, dry place

Health Claim

JBA® Hello Healthy Glucose
Coffee + Healing Herbs for Blood Glucose Support* With GlucoTrojan™, Reducose® & ABALife™ Fig Extract

Natural healing in a Coffee cup
Start the Day with Self-Care
Pour yourself a cup or our luscious JBA® Hello Healthy Glucose Hot Caffe Latte and sip your way to a healthier you. Made with rich, aromatic instant coffee, amino acids, and botanical extracts that help support blood glucose management, it’s the perfect way to kickstart your day.*

Maintain Normal Blood Sugar Levels*
With a botanical blend – featuring cordyceps, and ABALife™ fig extract – specially formulated to help maintain blood sugar levels already within the normal range.*

GlucoTrojan™ Block Starch Absorption*
With mangiferin from mango, white Reducose® a patented Mulberry leaf extract and Banana stem juice extract which blocks enzymes that break down starchy carbs, thus preventing their conversion into sugar.*

Optimize Your Energy*
With a morning boost from coffee, plus blood sugar support to help avoid energy crashes and support balanced energy levels throughout the day.*

* These statements have not been evaluated by the Food & Drug Administration. This product is not intended to diagnose, treat, cure, or prevent any disease.